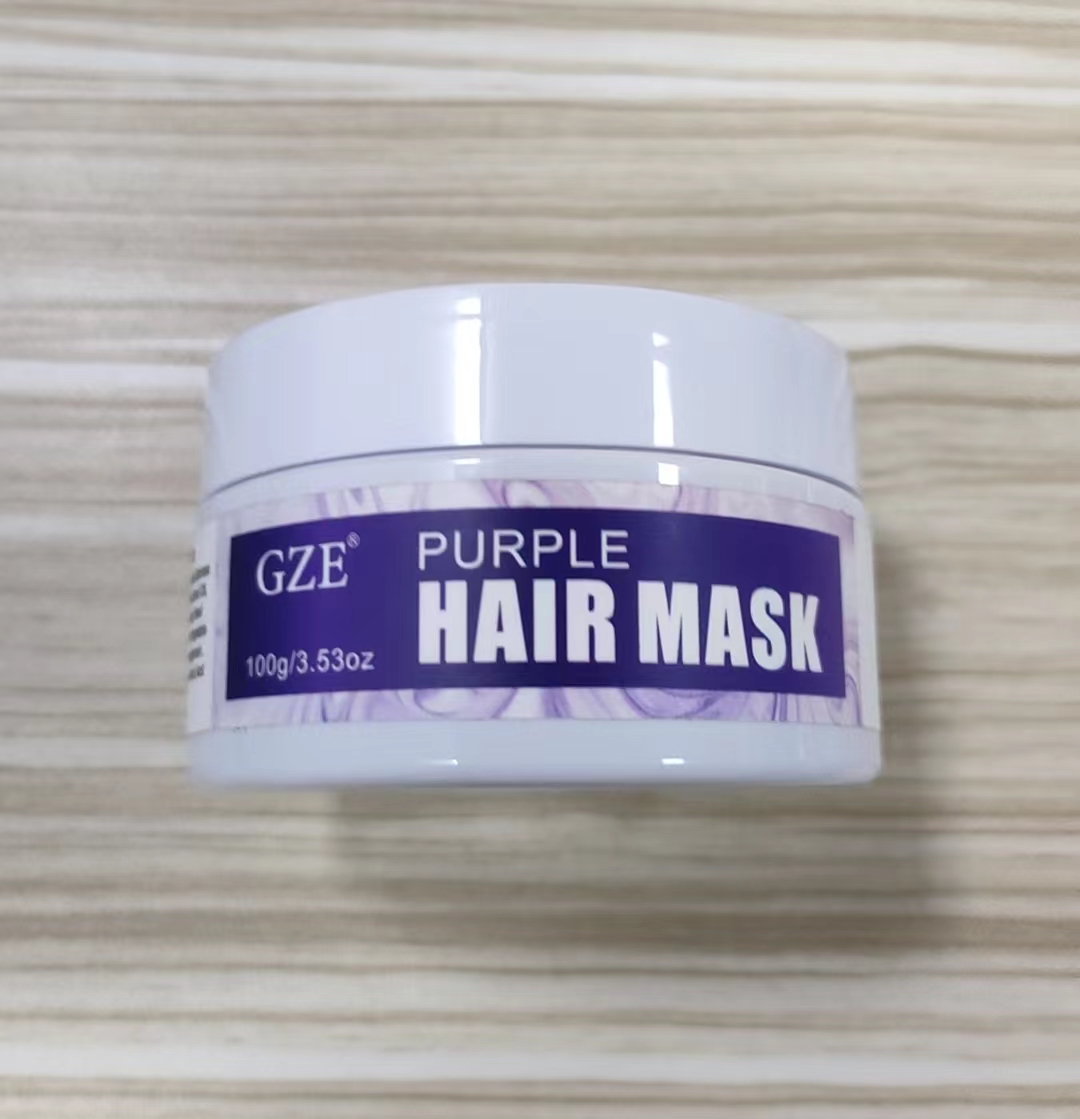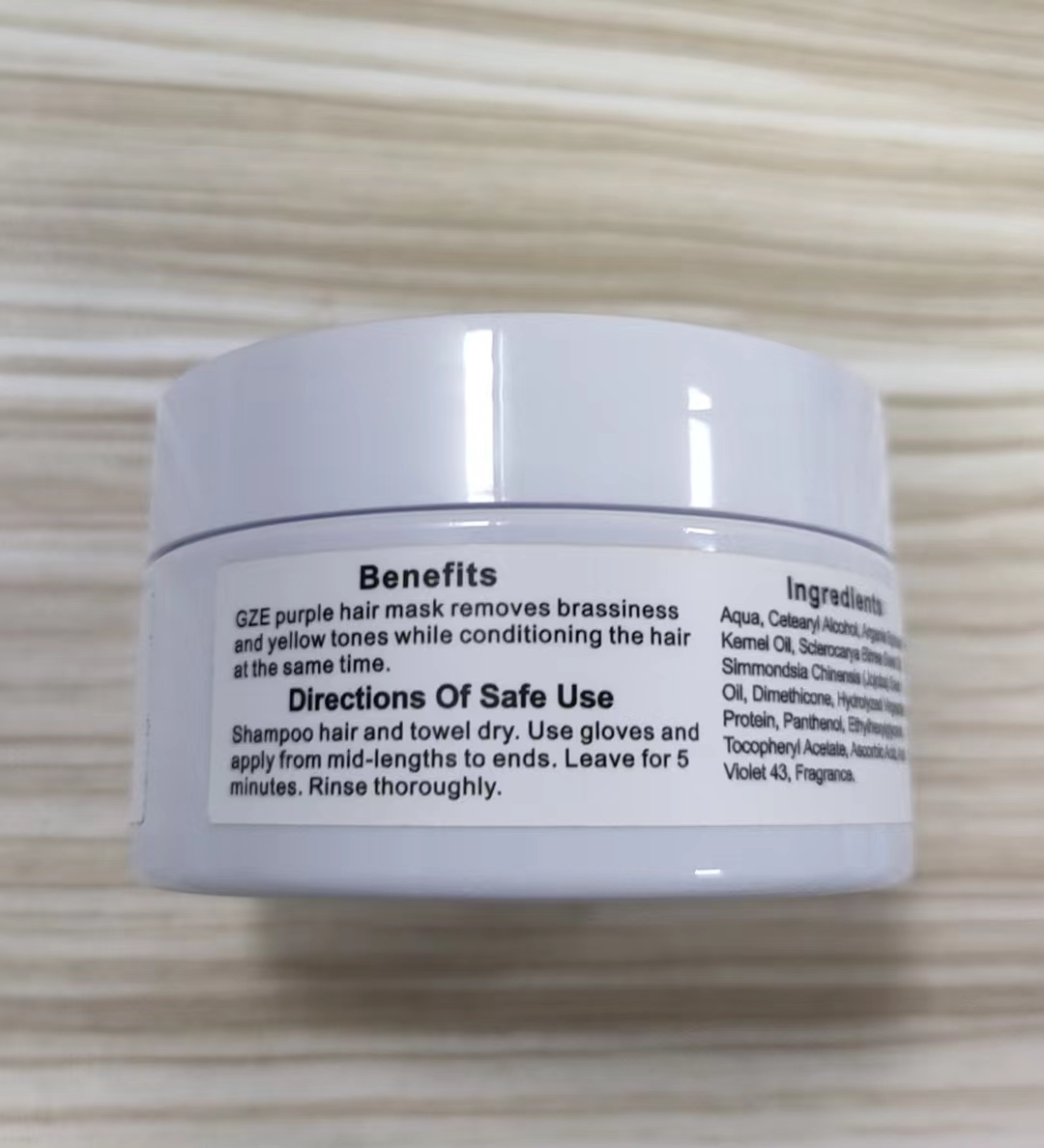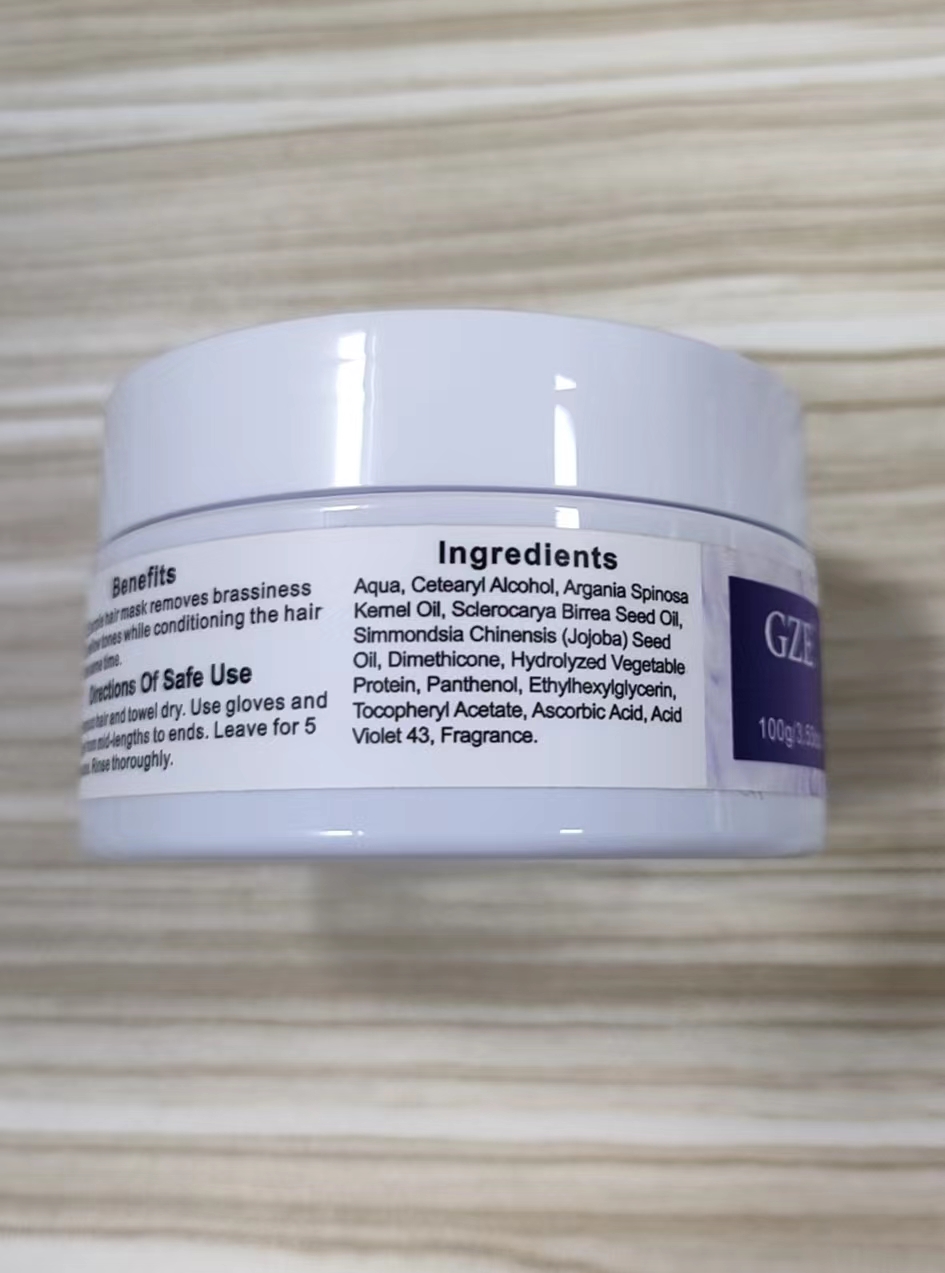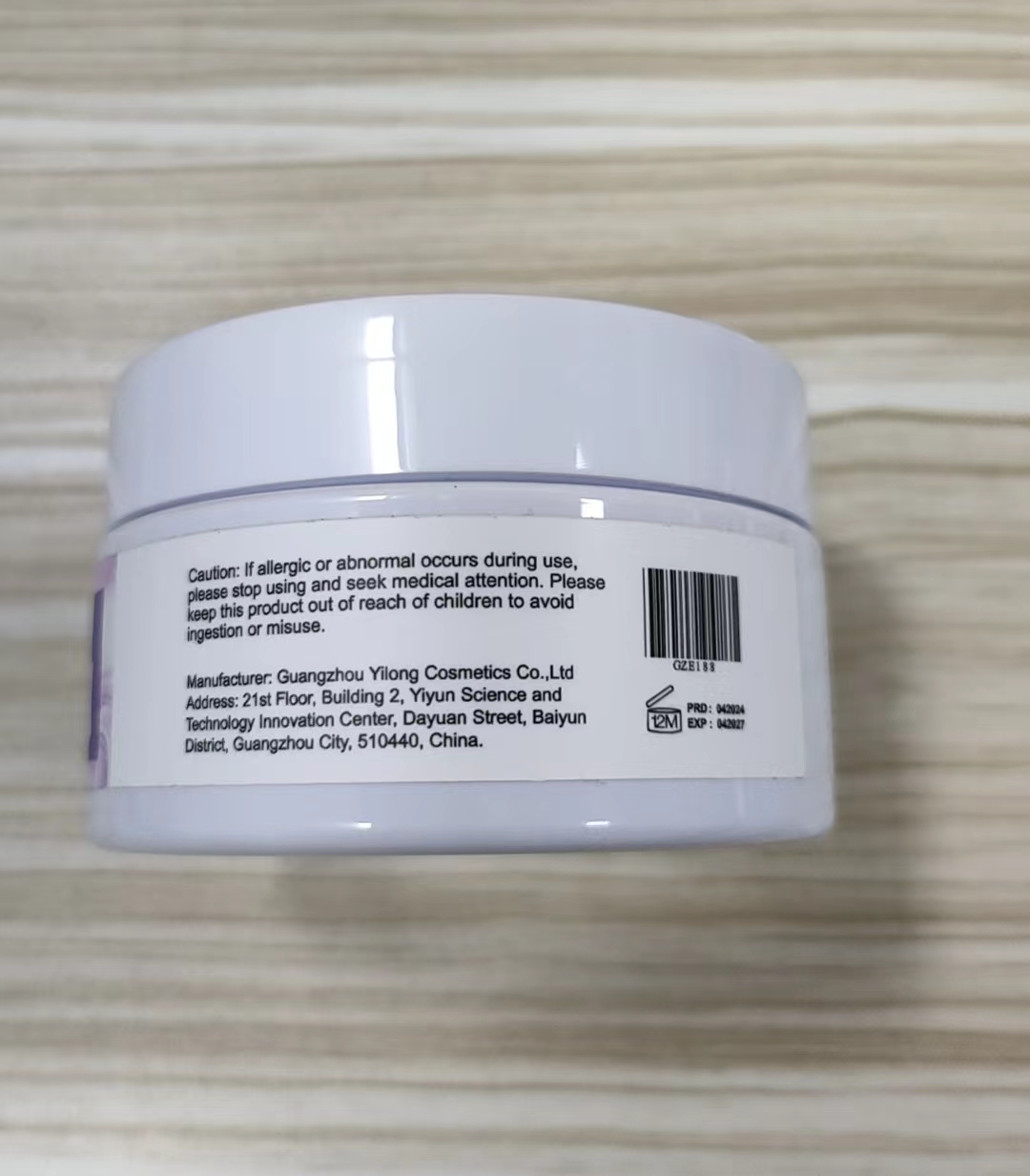 DRUG LABEL: GZE Purple HairMask
NDC: 83566-190 | Form: CREAM
Manufacturer: Guangzhou Yilong Cosmetics Co., Ltd
Category: otc | Type: HUMAN OTC DRUG LABEL
Date: 20240624

ACTIVE INGREDIENTS: SCLEROCARYA BIRREA SEED OIL 5 g/100 g; ARGANIA SPINOSA WHOLE 10 g/100 g; SIMMONDSIA CHINENSIS SEED 5 g/100 g
INACTIVE INGREDIENTS: ETHYLHEXYLGLYCERIN; FRAGRANCE 13576; .ALPHA.-TOCOPHEROL ACETATE, D-; ACID VIOLET 7; HYDROLYZED JOJOBA ESTERS (ACID FORM); WATER; CETEARYL STEARATE; DIMETHICONE; PANTHENOL; ASCORBIC ACID

GZE Purple Hair Mask

ACTIVE INGREDIENT

SCLEROCARYA BIRREA SEED OIL
SIMMONDSIA CHINENSIS SEED
ARGANIA SPINOSA WHOLE

INACTIVE INGREDIENT

ETHYLHEXYLGLYCERIN
FRAGRANCE 13576
ACID VIOLET 7
HYDROLYZED JOJOBA ESTERS (ACID FORM)
WATER
CETEARYL STEARATE
DIMETHICONE
PANTHENOL
.ALPHA.-TOCOPHEROL ACETATE.D-
ASCORBIC ACID

PURPOSE

Hair care

INDICATIONS AND USAGE

Shampoo hair and towel dry.Use gloves and apply from mid-lengths to ends. Leave for 5 minutes.Rinse thoroughly.

WARNINGS

For external use only.

Stop use and ask a doctor if rash occurs.

Do not use on damaged or broken skin.

When using this product keep out of eyes. Rinse with water to remove.

Keep out of reach of children. If swallowed, get medical help or contact a Poison Control Center right away.

DOSAGE AND ADMINISTRATION

Shampoo hair and towel dry.Use gloves and apply from mid-lengths to ends. Leave for 5 minutes.Rinse thoroughly.